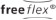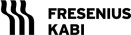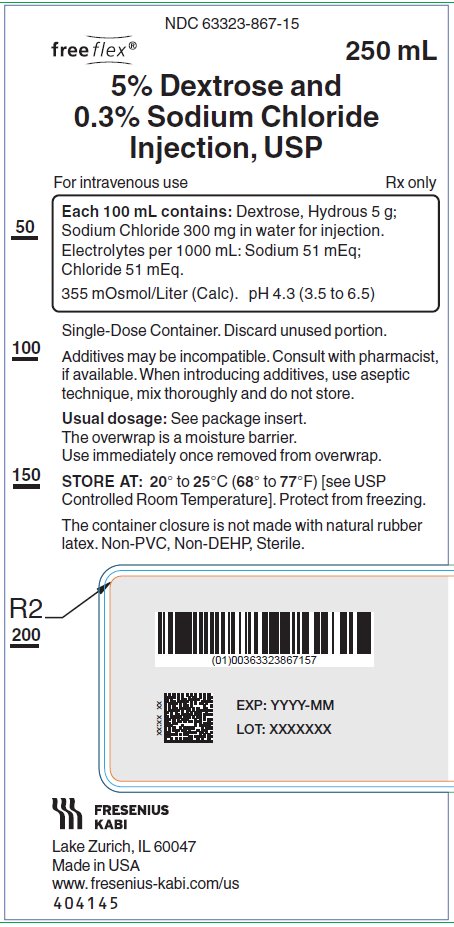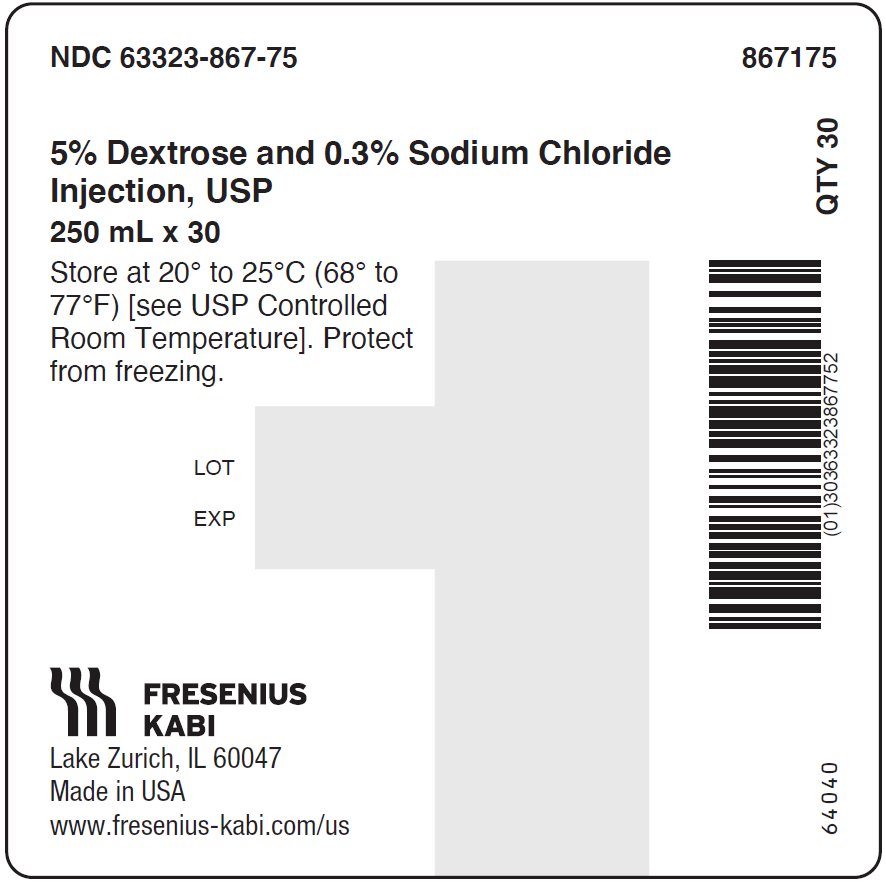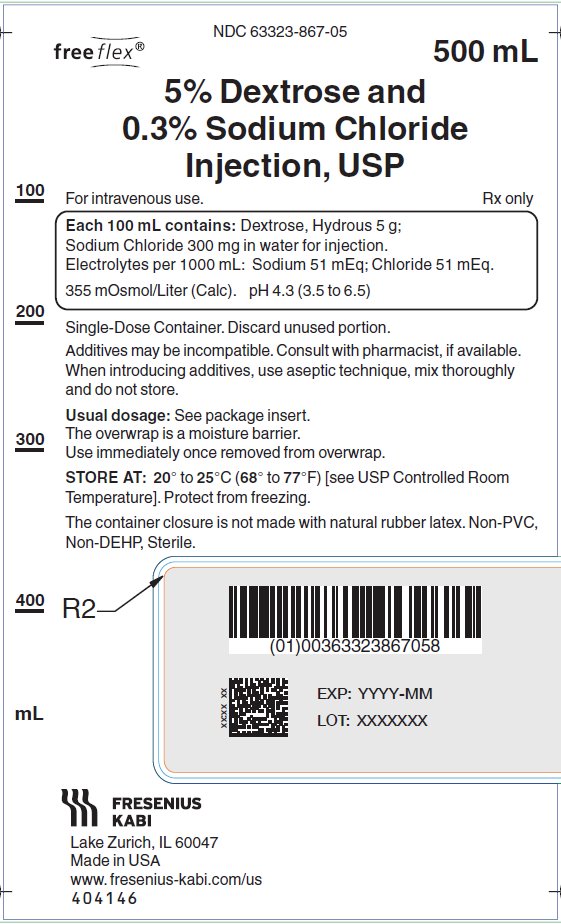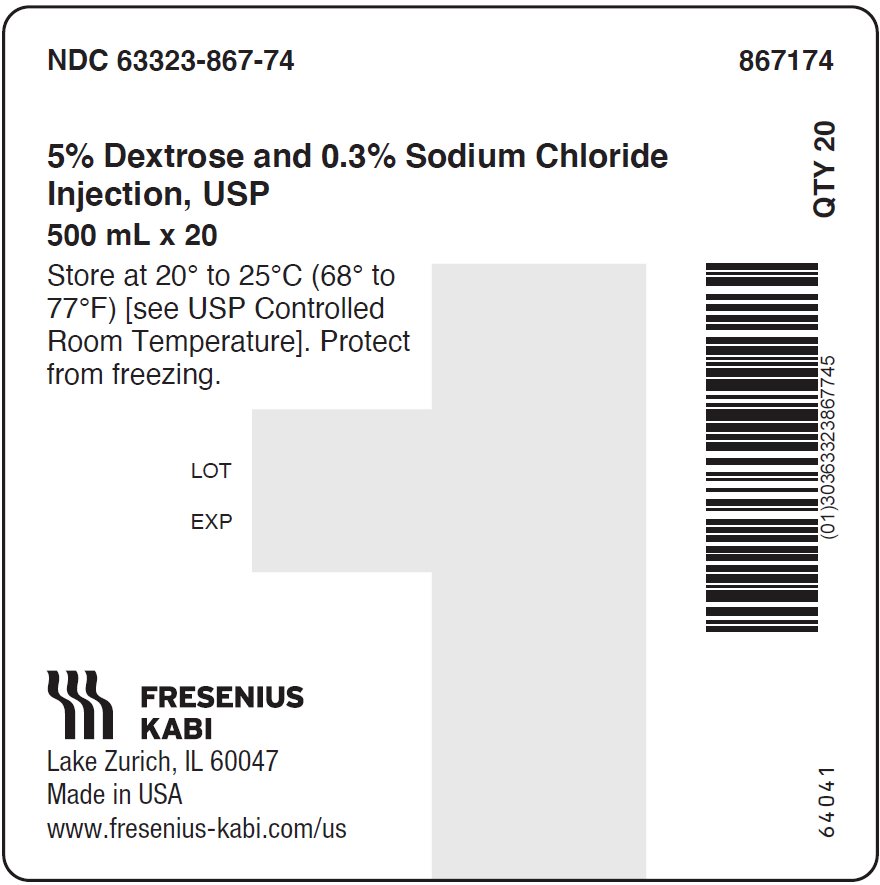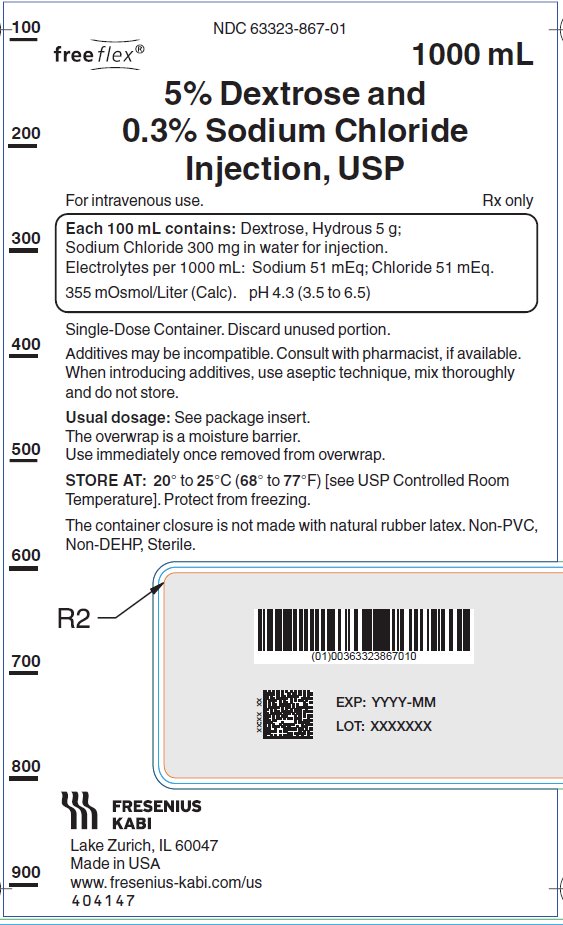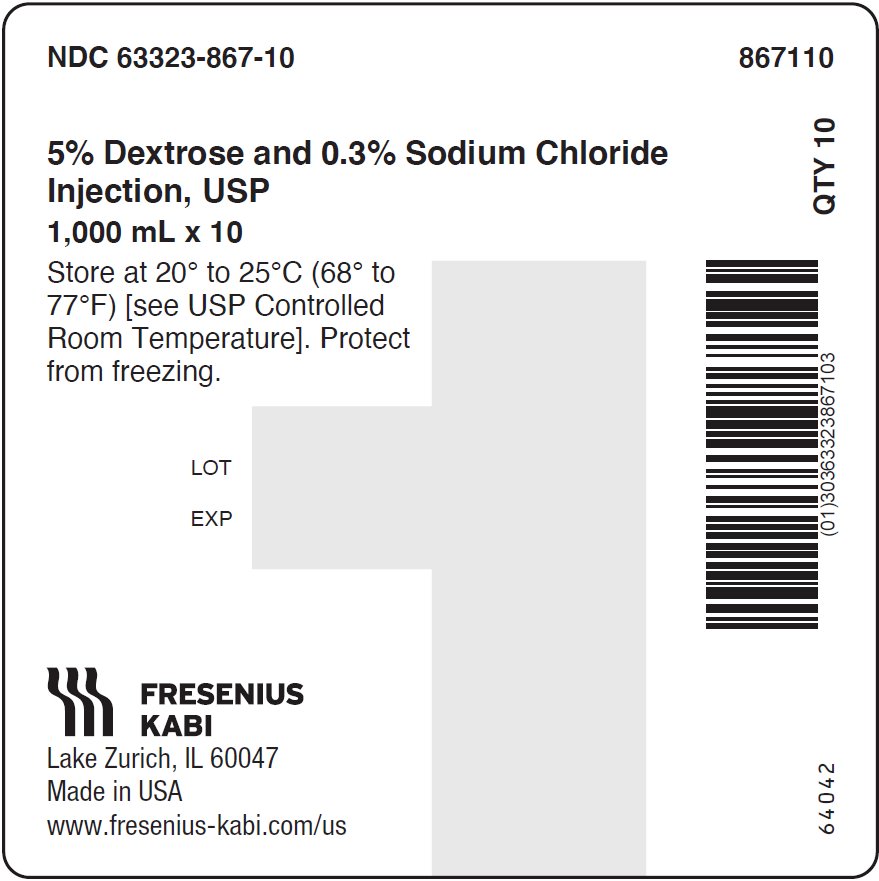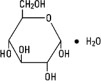 DRUG LABEL: Dextrose and Sodium Chloride
NDC: 63323-867 | Form: INJECTION, SOLUTION
Manufacturer: Fresenius Kabi USA, LLC
Category: prescription | Type: HUMAN PRESCRIPTION DRUG LABEL
Date: 20250403

ACTIVE INGREDIENTS: DEXTROSE MONOHYDRATE 5 g/100 mL; SODIUM CHLORIDE 0.3 g/100 mL
INACTIVE INGREDIENTS: WATER

DEXTROSE AND SODIUM CHLORIDE- dextrose monohydrate and sodium chloride injection, solution Dextrose and Sodium Chloride Injection, USP

Rx only

DESCRIPTION

Dextrose and Sodium Chloride Injection, USP solutions are sterile and nonpyrogenic. They are large volume parenteral solutions containing 5 grams per 100 mL of Dextrose and 0.3 grams per 100 mL of Sodium Chloride in water for injection intended for intravenous administration.

See Table for summary of content and characteristics of these solutions.

The solutions contain no bacteriostat, antimicrobial agent or added buffer and each is intended only as a single-dose injection. When smaller doses are required the unused portion should be discarded.

The solutions are parenteral fluid, nutrient and electrolyte replenishers.

Dextrose, USP is chemically designated D-glucose monohydrate (C6H12O6 • H2O), a hexose sugar freely soluble in water. It has the following structural formula:

Sodium Chloride, USP is chemically designated NaCl, a white crystalline powder freely soluble in water.

Water for Injection, USP is chemically designated H2O.

The flexible container is fabricated from a specially formulated non-plasticized, film containing polypropylene and thermoplastic elastomers (freeflex® bag). The amount of water that can permeate from the container into the overwrap is insufficient to affect the solution significantly. Solutions in contact with the flexible container can leach out certain of the container's chemical components in very small amounts within the expiration period. The suitability of the container material has been confirmed by tests in animals according to USP biological tests for plastic containers.

CLINICAL PHARMACOLOGY

When administered intravenously, these solutions provide a source of water, carbohydrate and electrolytes.

Solutions which provide combinations of hypotonic or isotonic concentrations of dextrose and of sodium chloride are suitable for parenteral maintenance or replacement of water and electrolyte requirements with minimal carbohydrate calories.

Solutions containing carbohydrate in the form of dextrose restore blood glucose levels and provide calories. Carbohydrate in the form of dextrose may aid in minimizing liver glycogen depletion and exerts a protein-sparing action. Dextrose injected parenterally undergoes oxidation to carbon dioxide and water.

Sodium chloride in water dissociates to provide sodium (Na^+) and chloride (Cl¯) ions. Sodium (Na^+) is the principal cation of the extracellular fluid and plays a large part in the therapy of fluid and electrolyte disturbances. Chloride (Cl¯) has an integral role in buffering action when oxygen and carbon dioxide exchange occurs in the red blood cells. The distribution and excretion of sodium (Na^+) and chloride (Cl¯) are largely under the control of the kidney which maintains a balance between intake and output.

Water is an essential constituent of all body tissues and accounts for approximately 70% of total body weight. Average normal adult daily requirements range from two to three liters (1.0 to 1.5 liters each for insensible water loss by perspiration and urine production). Water balance is maintained by various regulatory mechanisms. Water distribution depends primarily on the concentration of electrolytes in the body compartments and sodium (Na^+) plays a major role in maintaining physiologic equilibrium.

INDICATIONS AND USAGE

Intravenous solutions containing dextrose and sodium chloride are indicated for parenteral replenishment of fluid, minimal carbohydrate calories, and sodium chloride as required by the clinical condition of the patient.

CONTRAINDICATIONS

None known.

WARNINGS

Solutions containing sodium ions should be used with great care, if at all, in patients with congestive heart failure, severe renal insufficiency and in clinical states in which there exists edema with sodium retention.

Excessive administration of potassium-free solutions may result in significant hypokalemia.

In patients with diminished renal function, administration of solutions containing sodium ions may result in sodium retention.

The intravenous administration of these solutions can cause fluid and/or solute overloading resulting in dilution of serum electrolyte concentrations, overhydration, congested states or pulmonary edema.

The risk of dilutional states is inversely proportional to the electrolyte concentrations of administered parenteral solutions. The risk of solute overload causing congested states with peripheral and pulmonary edema is directly proportional to the electrolyte concentrations of such solutions.

PRECAUTIONS

Clinical evaluation and periodic laboratory determinations are necessary to monitor changes in fluid balance, electrolyte concentrations and acid-base balance during prolonged parenteral therapy or whenever the condition of the patient warrants such evaluation.

Solutions containing dextrose should be used with caution in patients with known subclinical or overt diabetes mellitus.

Caution must be exercised in the administration of parenteral fluids, especially those containing sodium ions to patients receiving corticosteroids or corticotropin.

Do not administer unless solution is clear and container is undamaged. Discard unused portion.

PREGNANCY

Pregnancy Category C. Animal reproduction studies have not been conducted with dextrose or sodium chloride. It is also not known whether dextrose or sodium chloride can cause fetal harm when administered to a pregnant woman or can affect reproduction capacity. Dextrose or sodium chloride should be given to a pregnant woman only if clearly needed.

PEDIATRIC USE

Pediatric Use. The safety and effectiveness in the pediatric population are based on the similarity of the clinical conditions of the pediatric and adult populations. In neonates or very small infants, the volume of fluid may affect fluid and electrolyte balance.

Frequent monitoring of serum glucose concentrations is required when dextrose is prescribed to pediatric patients, particularly neonates and low birth weight infants.

In very low birth weight infants, excessive or rapid administration of dextrose injection may result in increased serum osmolality and possible intracerebral hemorrhage.

GERIATRIC USE

Geriatric Use. An evaluation of current literature revealed no clinical experience identifying differences in response between elderly and younger patients. In general, dose selection for an elderly patient should be cautious, usually starting at the low end of the dosing range, reflecting the greater frequency of decreased hepatic, renal, or cardiac function, and of concomitant disease or other drug therapy. Sodium ions are known to be substantially excreted by the kidney, and the risk of toxic reactions may be greater in patients with impaired renal function. Because elderly patients are more likely to have decreased renal function, care should be taken in dose selection, and it may be useful to monitor renal function.

ADVERSE REACTIONS

Reactions which may occur because of the solution or the technique of administration include febrile response, infection at the site of injection, venous thrombosis or phlebitis extending from the site of injection, extravasation and hypervolemia.

If an adverse reaction does occur, discontinue the infusion, evaluate the patient, institute appropriate therapeutic countermeasures and save the remainder of the fluid for examination if deemed necessary.

OVERDOSAGE

In the event of overhydration or solute overload, re-evaluate the patient and institute appropriate corrective measures. See WARNINGS, PRECAUTIONS, and ADVERSE REACTIONS.

DOSAGE AND ADMINISTRATION

The dose is dependent upon the age, weight and clinical condition of the patient.

As reported in the literature, the dosage and constant infusion rate of intravenous dextrose must be selected with caution in pediatric patients, particularly neonates and low birth weight infants, because of the increased risk of hyperglycemia/hypoglycemia.

Parenteral drug products should be inspected visually for particulate matter and discoloration prior to administration, whenever solution and container permit. See PRECAUTIONS.

Drug Interactions

Additives may be incompatible. Consult with pharmacist, if available. When introducing additives, use aseptic technique, mix thoroughly and do not store.

INSTRUCTIONS FOR USE:

Check flexible container solution composition, lot number, and expiry date.

Do not remove solution container from its overwrap until immediately before use. Use sterile equipment and aseptic technique.

To Open

1. Turn solution container over so that the text is face down. Using the pre-cut corner tabs, peel open the overwrap and remove solution container.
2. Check the solution container for leaks by squeezing firmly. If leaks are found, or if the seal is not intact, discard the solution.
3. Do not use if the solution is cloudy or a precipitate is present.

To Add Medication

1. Identify WHITE Additive Port with arrow pointing toward container.
2. Immediately before injecting additives, break off WHITE Additive Port Cap with the arrow pointing toward container.
3. Hold base of WHITE Additive Port horizontally.
4. Insert needle horizontally through the center of WHITE Additive Port's septum and inject additives.
5. Mix container contents thoroughly. For high density medication such as potassium chloride, squeeze ports while ports are upright and mix thoroughly.

Preparation for Administration

1. Immediately before inserting the infusion set, break off BLUE Infusion Port Cap with the arrow pointing away from container.
2. Use a non-vented infusion set or close the air-inlet on a vented set.
3. Close the roller clamp of the infusion set.
4. Hold the base of BLUE Infusion Port.
5. Insert spike through BLUE Infusion Port by rotating wrist slightly until the spike is inserted.

NOTE: See full directions accompanying administration set.

WARNING: Do not use flexible container in series connections.

HOW SUPPLIED

Dextrose and Sodium Chloride Injection, USP are supplied in single-dose flexible plastic containers in various sizes as shown in the accompanying Table.

Content and Characteristics
 |  |  |  | Grams/100 mL |  | Per 1000 mL
Product Code | Unit of Sale | Each | Product | Dextrose (hydrous) | Sodium Chloride | Sodium Na^+ | Chloride Cl^– | Caloric | Tonicity | Osmolarity mOsmol/L (calc) | pH | Container
867175 | 63323-867-75 | 63323-867-15 | 5% Dextrose and 0.3% Sodium Chloride Inj., USP | 5 | 0.3 | 51 mEq | 51 mEq | 170 | Hypertonic | 355 | 4.3 (3.5 to 6.5) | 250 mL Bag
867174 | 63323-867-74 | 63323-867-05 | 5% Dextrose and 0.3% Sodium Chloride Inj., USP | 5 | 0.3 | 51 mEq | 51 mEq | 170 | Hypertonic | 355 | 4.3 (3.5 to 6.5) | 500 mL Bag
867110 | 63323-867-10 | 63323-867-01 | 5% Dextrose and 0.3% Sodium Chloride Inj., USP | 5 | 0.3 | 51 mEq | 51 mEq | 170 | Hypertonic | 355 | 4.3 (3.5 to 6.5) | 1000 mL Bag

The container closure is not made with natural rubber latex. Non-PVC, Non-DEHP, Sterile.

Protect from freezing. Store at 20° to 25°C (68° to 77°F). [See USP Controlled Room Temperature.].

Manufactured for:

Lake Zurich, IL 60047

www.fresenius-kabi.com/us

PACKAGE LABEL – PRINCIPAL DISPLAY – Dextrose and Sodium Chloride 250 mL Bag Label

NDC 63323-867-15

freeflex® 250 mL

5% Dextrose and
0.3% Sodium Chloride
Injection, USP

For intravenous use Rx only

PACKAGE LABEL – PRINCIPAL DISPLAY – Dextrose and Sodium Chloride 250 mL Case Label

NDC 63323-867-75 867175

5% Dextrose and 0.3% Sodium Chloride
Injection, USP
250 mL x 30

Store at 20° to 25°C (68° to 77°F) [see USP Controlled Room Temperature]. Protect from freezing.

PACKAGE LABEL – PRINCIPAL DISPLAY – Dextrose and Sodium Chloride 500 mL Bag Label

NDC 63323-867-05

freeflex® 500 mL

5% Dextrose and
0.3% Sodium Chloride
Injection, USP

For intravenous use Rx only

PACKAGE LABEL – PRINCIPAL DISPLAY – Dextrose and Sodium Chloride 500 mL Case Label

NDC 63323-867-74 867174

5% Dextrose and 0.3% Sodium Chloride
Injection, USP
500 mL x 20

Store at 20° to 25°C (68° to 77°F) [see USP Controlled Room Temperature]. Protect from freezing.

PACKAGE LABEL – PRINCIPAL DISPLAY – Dextrose and Sodium Chloride 1000 mL Bag Label

NDC 63323-867-01

freeflex® 1000 mL

5% Dextrose and
0.3% Sodium Chloride
Injection, USP

For intravenous use Rx only

PACKAGE LABEL – PRINCIPAL DISPLAY – Dextrose and Sodium Chloride 1000 mL Case Label

NDC 63323-867-10 867110

5% Dextrose and 0.3% Sodium Chloride
Injection, USP
1,000 mL x 10

Store at 20° to 25°C (68° to 77°F) [see USP Controlled Room Temperature]. Protect from freezing.